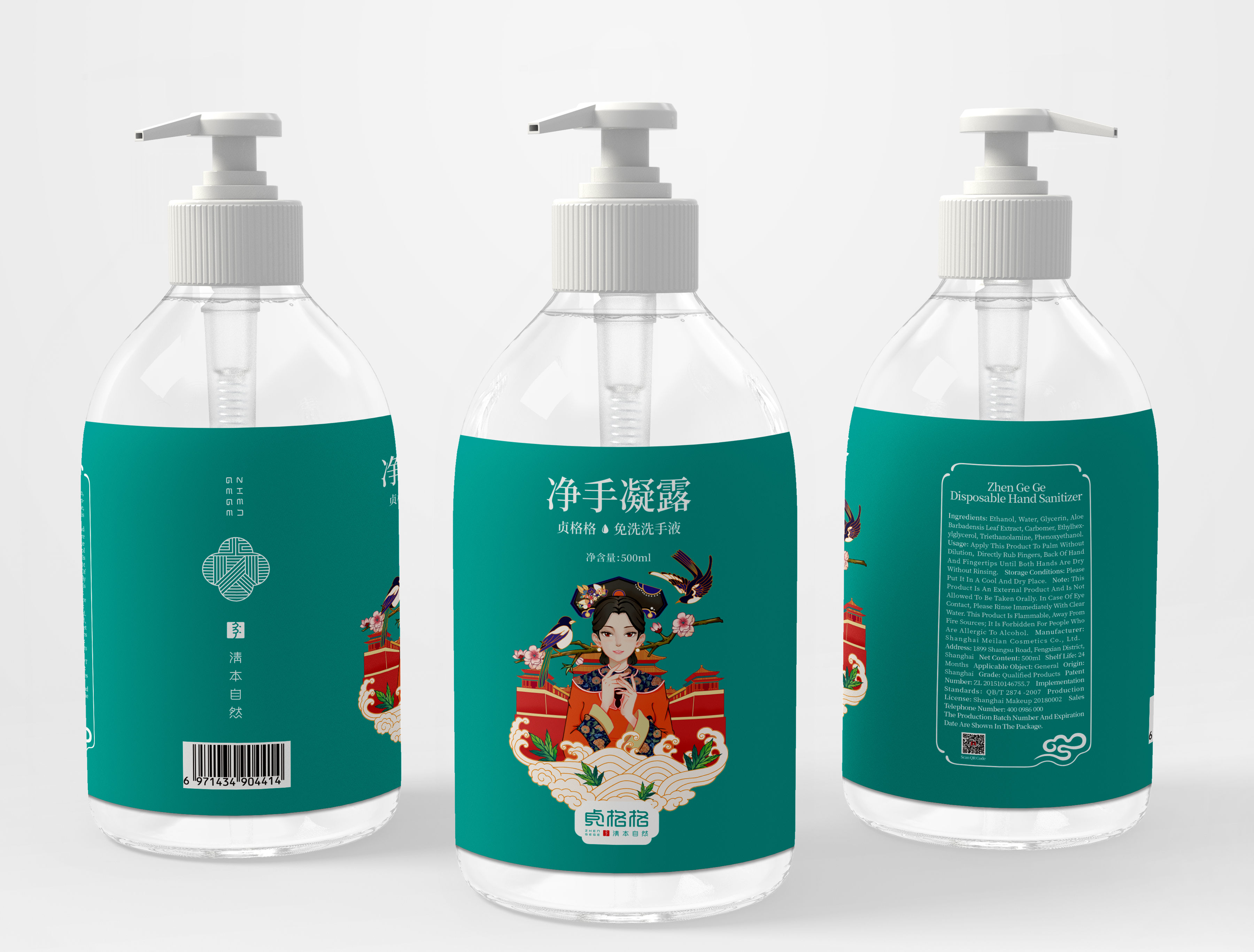 DRUG LABEL: Zhen Ge Ge Disposable Hand Sanitizer
NDC: 41597-001 | Form: GEL
Manufacturer: Shanghai Meilan Cosmetics Co., Ltd.
Category: otc | Type: HUMAN OTC DRUG LABEL
Date: 20200424

ACTIVE INGREDIENTS: ALCOHOL 375 mL/500 mL
INACTIVE INGREDIENTS: WATER

DOSAGE AND ADMINISTRATION

Please Put It In A Cool And Dry Place.

INACTIVE INGREDIENT

Deionized water

INDICATIONS AND USAGE

Apply This Produet To Palm Without Dilution, Directly Rub Fingers, Back of Hand And Fingertips Until Both Hands Are Dry Without Rinsing.

ACTIVE INGREDIENT

Alcohol

keep out of children

PURPOSE

Disinfection
Sterilization
No Rinseing

WARNINGS

This Product Is An External Product And Is Not Allowed To Be Taken Orally. In Case of Eye Contact, Please Rinse Immediately With Clear Water. This Product Is Flammable, Away From Fire.